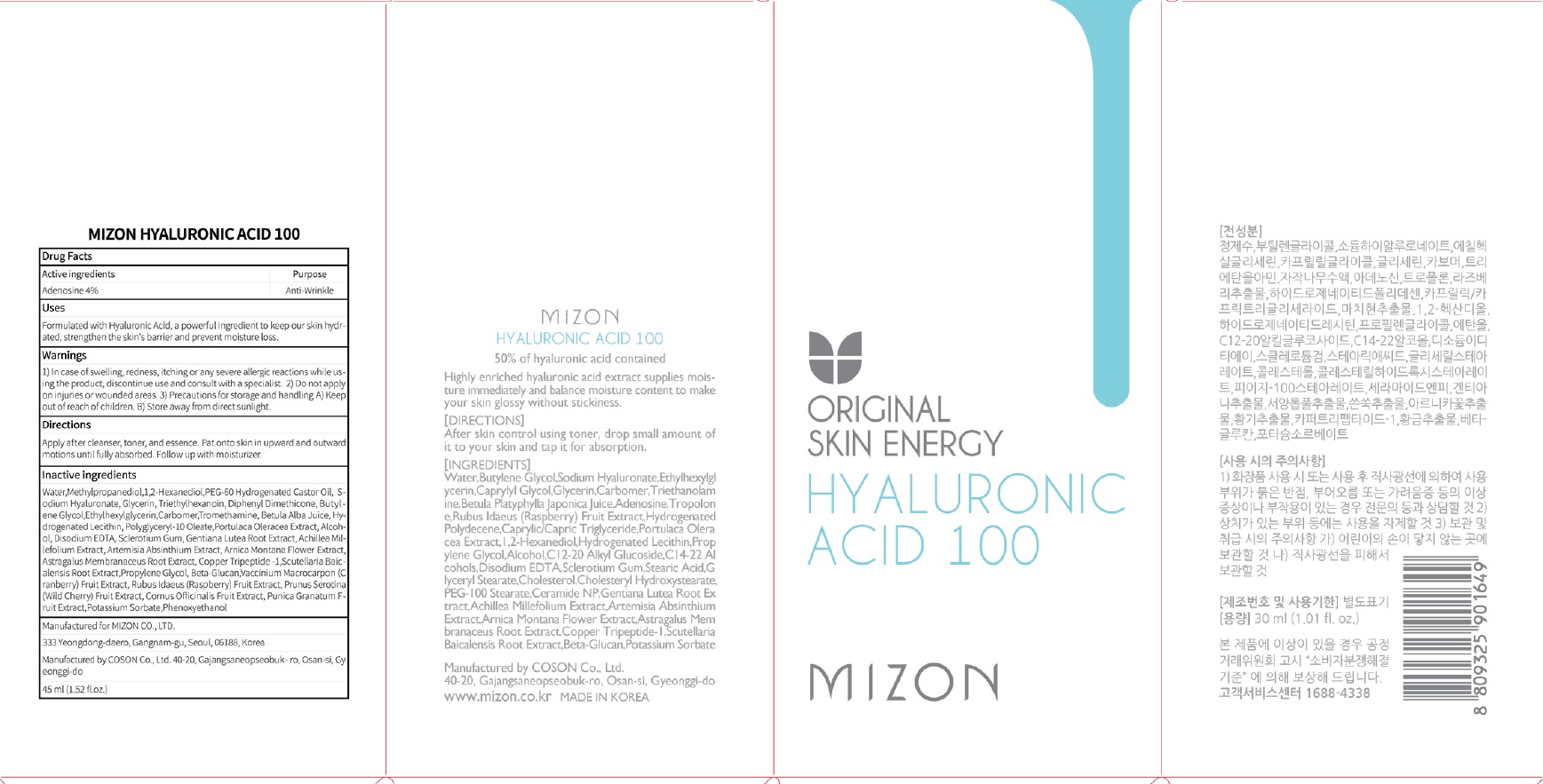 DRUG LABEL: MIZON HYALURONIC ACID 100
NDC: 57718-290 | Form: LIQUID
Manufacturer: MIZON CO.,LTD.
Category: otc | Type: HUMAN OTC DRUG LABEL
Date: 20180724

ACTIVE INGREDIENTS: Adenosine 0.012 g/30 mL
INACTIVE INGREDIENTS: Water; Methylpropanediol

ACTIVE INGREDIENT

Active ingredients: Adenosine 0.04%

INACTIVE INGREDIENT

Inactive ingredients:

Water,Methylpropanediol,1,2-Hexanediol,PEG-60 Hydrogenated Castor Oil,Sodium Hyaluronate,Glycerin,Triethylhexanoin,Diphenyl Dimethicone,Butylene Glycol,Ethylhexylglycerin,Carbomer,Tromethamine, Betula Alba Juice, ,Hydrogenated Lecithin, Polyglyceryl-10 Oleate,Portulaca Oleracea Extract,Alcohol,Disodium EDTA,Sclerotium Gum,Gentiana Lutea Root Extract,Achillea Millefolium Extract,Artemisia Absinthium Extract,Arnica Montana Flower Extract,Astragalus Membranaceus Root Extract,Copper Tripeptide -1,Scutellaria Baicalensis Root Extract,Propylene Glycol, Beta-Glucan,Vaccinium Macrocarpon (Cranberry) Fruit Extract,Rubus Idaeus (Raspberry) Fruit Extract,Prunus Serotina (Wild Cherry) Fruit Extract,Cornus Officinalis Fruit Extract,Punica Granatum Fruit Extract,Potassium Sorbate,Phenoxyethanol

PURPOSE

Purpose: Anti Wrinkle

WARNINGS

1) In case of swelling, redness, itching or any severe allergic reactions while using the product,discontinue use and consult with a specialist. 2) Do not apply on injuries or wounded areas. 3) Precautions for storage and handling A) Keep out of reach of children. B) Store away from direct sunlight.

KEEP OUT OF REACH OF CHILDREN

Uses

Formulated with Hyaluronic Acid, a powerful ingredient to keep our skin hydrated, strengthen the skin's barrier and prevent moisture loss.

Directions

Apply after cleanser, toner, and essence. Pat onto skin in upward and outward motions until fully absorbed. Follow up with moisturizer.